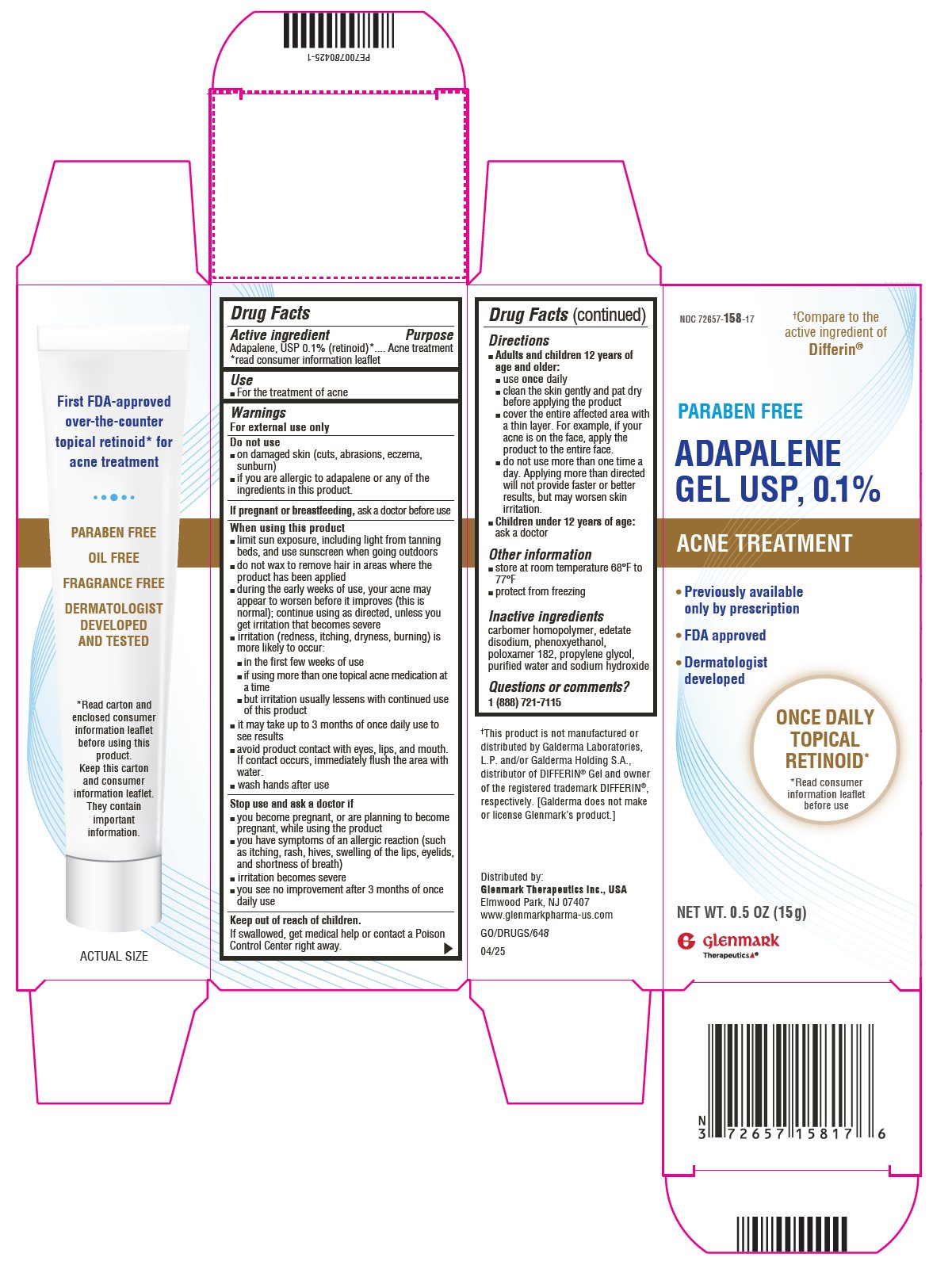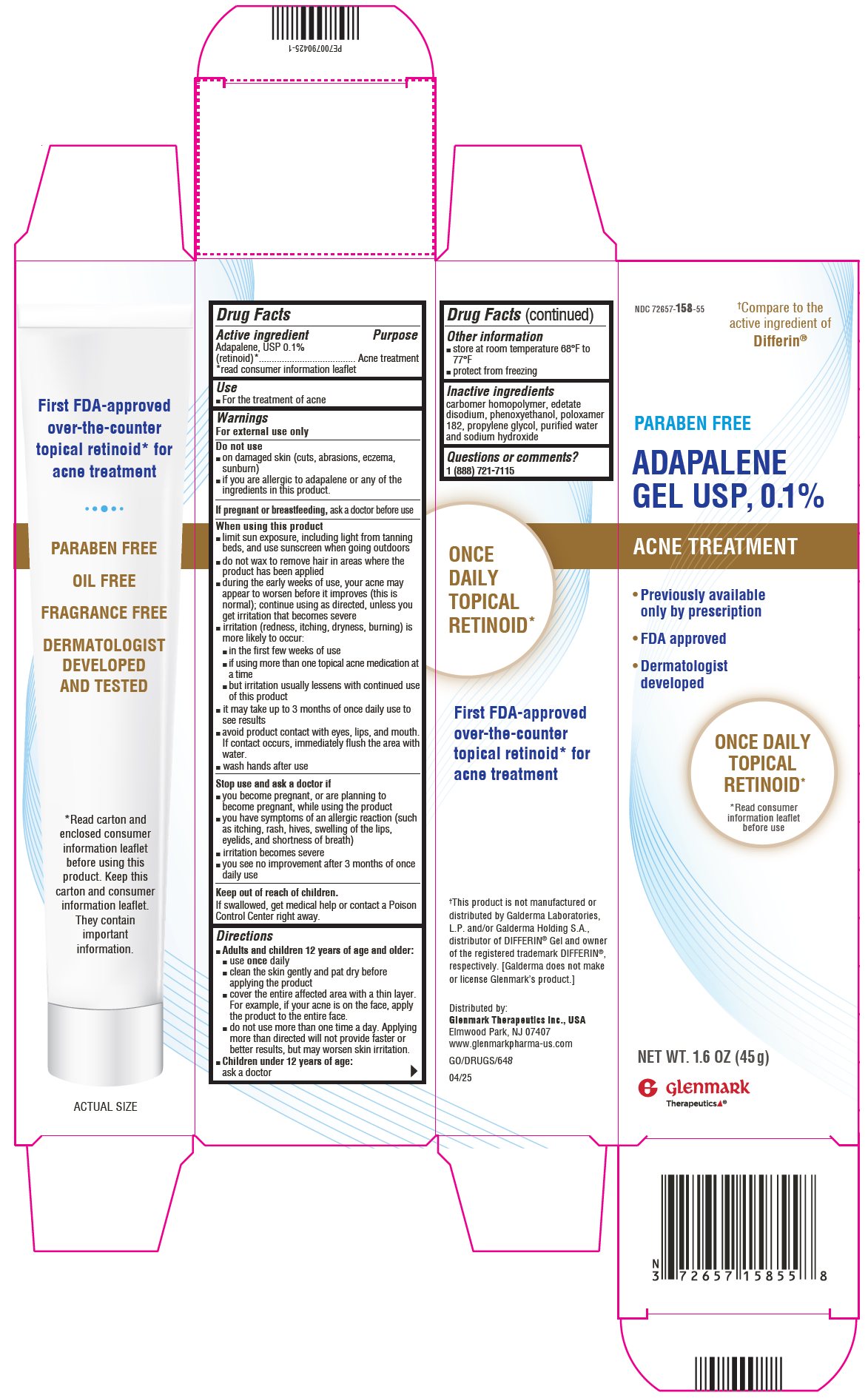 DRUG LABEL: Adapalene
NDC: 72657-158 | Form: GEL
Manufacturer: GLENMARK THERAPEUTICS INC., USA
Category: otc | Type: HUMAN OTC DRUG LABEL
Date: 20260131

ACTIVE INGREDIENTS: ADAPALENE 1 mg/1 g
INACTIVE INGREDIENTS: CARBOMER HOMOPOLYMER TYPE C (ALLYL PENTAERYTHRITOL CROSSLINKED); EDETATE DISODIUM; POLOXAMER 182; PROPYLENE GLYCOL; WATER; SODIUM HYDROXIDE; PHENOXYETHANOL

Drug Facts

Active ingredient

Adapalene, USP 0.1% (retinoid)*

*read consumer Information leaflet

Purpose

Acne treatment

Use

- For the treatment of acne

Warnings

For external use only

Do not use

- on damaged skin (cuts, abrasions, eczema, sunburn)
- if you are allergic to adapalene or any of the ingredients in this product

If pregnant or breastfeeding, ask a doctor before use

When using this product

- limit sun exposure, including light from tanning beds, and use sunscreen when going outdoors
- do not wax to remove hair in areas where the product has been applied
- during the early weeks of use, your acne may appear to worsen before it improves (this is normal); continue using as directed, unless you get irritation that becomes severe
- irritation (redness, itching, dryness, burning) is more likely to occur:
- the first few weeks of use
- if using more than one topical acne medication at a time
- but irritation usually lessens with continued use of this product
- it may take up to 3 months of once daily use to see results
- avoid product contact with eyes, lips, and mouth. If contact occurs, immediately flush the area with water.
- wash hands after use

Stop use and ask doctor if

- you become pregnant, or are planning to become pregnant, while using the product
- you have symptoms of an allergic reaction (such as itching, rash, hives, swelling of the lips, eyelids, and shortness of breath)
- irritation becomes severe
- you see no improvement after 3 months of once daily use

Keep out of reach of children.

If swallowed, get medical help or contact a Poison Control Center right away.

Directions

- Adults and children 12 years of age and older:
- use once daily
- clean the skin gently and pat dry before applying the product
- cover the entire affected area with a thin layer. For example, if your acne is on the face, apply the product to the entire face.
- do not use more than one time a day. Applying more than directed will not provide faster or better results, but may worsen skin irritation.
- Children under 12 years of age: ask a doctor

Other information

- store at room temperature 68°F to 77°F
- protect from freezing

Inactive Ingredients

carbomer homopolymer, edetate disodium, phenoxyethanol, poloxamer 182, propylene glycol, purified water and sodium hydroxide

Questions or comments?

1 (888) 721-7115

Patient Leaflet

ADAPALENE GEL USP, 0.1%

ACNE TREATMENT

Frequently Asked Questions

What is adapalene gel 0.1% and what is it used for?

- Adapalene gel 0.1% is a topical retinoid medication used for the treatment of acne in people age 12 years and older.
- Use only one time a day.

What should I know before using the product?

- If pregnant or breastfeeding, ask a doctor before use.
- Some other retinoid drugs have been shown to cause birth defects. There is no specific evidence that adapalene gel 0.1% causes birth defects in humans when used topically as directed.
- Do not use adapalene gel 0.1% if you are allergic to adapalene or any of the ingredients in this product.
- Keep out of reach of children. If swallowed, get medical help or contact a Poison Control Center right away.

How often do I apply the product?

- Apply this product only one time a day and try to apply the product at the same time each day.

How do I apply the product?

- Gently clean the affected areas using a mild (non-irritating) cleanser and pat dry.
- Apply adapalene gel 0.1% as a thin layer to the affected areas of the skin only one time a day. For example, if you get acne on the face, clean, dry and apply the product to the entire face. Adapalene gel 0.1% is not a spot treatment and should not be used to treat a single pimple.
- Avoid product contact with eyes, lips and mouth. If contact occurs, immediately flush the area with water.
- Do not apply product to damaged skin (cuts, abrasions, eczema, or sunburn).
- Wash hands after use.

How long will it take for adapalene gel 0.1% to work?

- It may take up to 3 months of daily use for results to appear.
- Do not use more than one time a day. Applying more than directed will not provide faster or better results, but may worsen skin irritation.

What do I do if I need to be in the sun?

- When possible, limit sun exposure, including light from tanning beds.
- When going outdoors, use a sunscreen as labeled. Your skin may be more sensitive while using adapalene gel 0.1%. If you use this product during the day, allow it to dry before applying sunscreen.

Can I use a moisturizer if my skin is dry?

- Yes, use of a moisturizer may help decrease dryness and other signs of irritation. Avoid products containing alpha hydroxy or glycolic acids which may worsen irritation.

When is my skin most likely to become irritated? And what do I do?

- Irritation (redness, itching, dryness, burning) is more likely to occur:
- In the first few weeks of use.
- if using abrasive skin cleansers, products with drying effects or more than one topical acne medication at a time. You may want to delay starting adapalene gel 0.1% until any irritation from using the other product(s) has gone away.
- Moisturizers may be used.
- Irritation usually lessens after 4 weeks of continued use.

What do I do if my skin becomes severely irritated?

- If irritation becomes severe (overly bothersome), stop use and ask a doctor before using the product again.

Can I remove unwanted facial hair by waxing while using this product?

- Do not use wax to remove hair in areas where the product has been applied because it may worsen skin irritation.

What ingredients are used in adapalene gel 0.1%?

- Adapalene gel 0.1% contains:

The active ingredient is adapalene 0.1%. The other ingredients are: carbomer homopolymer, edetate disodium, phenoxyethanol, poloxamer 182, propylene glycol, purified water and sodium hydroxide.

How should I store this product?

- Adapalene gel 0.1% should be stored at room temperature [68° to 77°F]. Protect from freezing.
- Do not use the product after the expiry date marked on the crimp of the tube.

Other Questions? Where can I get more information?

Phone: 1 (888) 721-7115

04/25

Package/Label Principal Display Panel

NDC 72657-158-17

Adapalene Gel USP, 0.1%

NET WT. 0.5 OZ (15 g)

Package/Label Principal Display Panel

NDC 72657-158-55

Adapalene Gel USP, 0.1%

NET WT. 1.6 OZ (45 g)